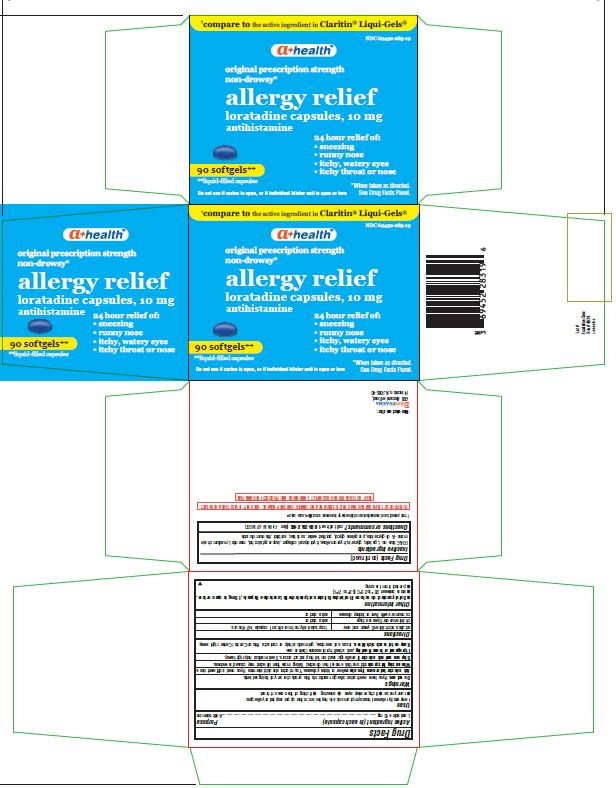 DRUG LABEL: LORATADINE
NDC: 69452-283 | Form: CAPSULE, LIQUID FILLED
Manufacturer: Bionpharma Inc.
Category: otc | Type: HUMAN OTC DRUG LABEL
Date: 20241223

ACTIVE INGREDIENTS: LORATADINE 10 mg/1 1
INACTIVE INGREDIENTS: CAPRYLIC/CAPRIC ACID; FD&C BLUE NO. 1; GELATIN; GLYCERIN; HYPROMELLOSES; HYDROLYSED BOVINE COLLAGEN (ENZYMATIC; 2000-5000 MW); ISOPROPYL ALCOHOL; MANNITOL; PROPYLENE GLYCOL; WATER; SORBITAN; SORBITOL; TITANIUM DIOXIDE

Drug Facts

Active ingredient (in each capsule)

Loratadine 10 mg

Purpose

Antihistamine

Uses

temporarily relieves these symptoms due to hay fever or other upper respiratory allergies:

- runny nose
- itchy, watery eyes
- sneezing
- itching of the nose or throat

Warnings

Do not use

if you have ever had an allergic reaction to this product or any of its ingredients.

Ask a doctor before use if you have

liver or kidney disease. Your doctor should determine if you need a different dose.

When using this product

do not take more than directed. Taking more than directed may cause drowsiness.

Stop use and ask a doctor if

an allergic reaction to this product occurs. Seek medical help right away.

If pregnant or breast-feeding,

ask a health professional before use.

Keep out of reach of children.

In case of overdose, get medical help or contact a Poison Control Center right away.

Directions

adults and children 6 years and over | 1 capsule daily; not more than 1 capsule in 24 hours
children under 6 years of age | ask a doctor
consumers with liver or kidney disease | ask a doctor

Other information

- Tamper-evident: do not use if foil seal under cap, printed with “Sealed for your protection” is missing, open or broken. (For Bottle Labels and Cartons)
- Safety sealed: do not use if individual blister unit printed with Loratadine Capsule, 10 mg is open or torn. (For Blister Carton)
- store between 20° to 25°C (68° to 77°F)
- protect from freezing

Inactive ingredients

FD&C blue no.1, gelatin, glycerin, hypromellose, hydrolyzed collagen, isopropyl alcohol, mannitol, medium chain mono- & di-glycerides, propylene glycol, purified water, sorbitan, sorbitol, titanium dioxide

Questions or comments?

call toll free 1-888-235-2466 (Mon - Fri 9AM - 5PM EST)

†This product is not manufactured or distributed by the owners of Claritin® LIQUI-GELS®.

Blister carton contain the following:

THIS PRODUCT IS PACKAGED IN A CHILD-RESISTANT AND TAMPER EVIDENT PACKAGE. USE ONLY IF BLISTERS ARE INTACT.
KEEP OUTER CARTON FOR COMPLETE WARNINGS AND PRODUCT INFORMATION.

Do not use if carton is open, or if individual blister unit is open or torn

Manufactured for:

Bionpharma Inc.

600 Alexander Road,

Princeton, NJ 08540